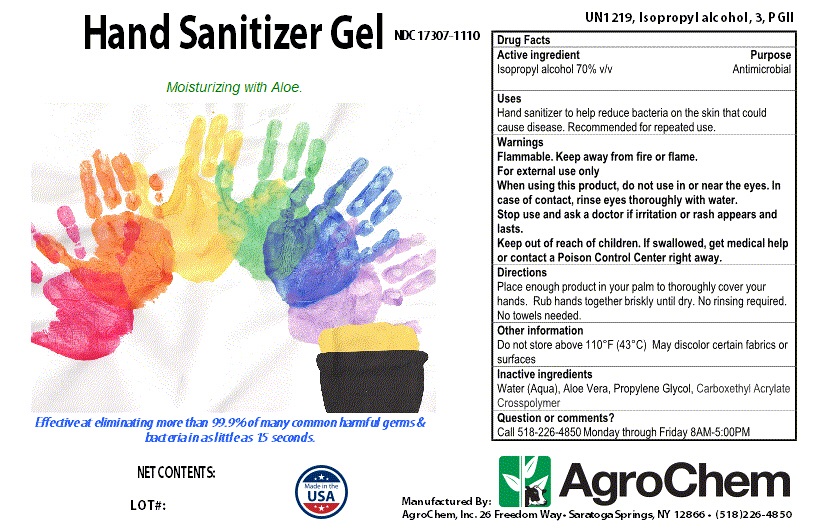 DRUG LABEL: Hand Sanitizer Gel
NDC: 17307-1110 | Form: GEL
Manufacturer: AgroChem Inc
Category: otc | Type: HUMAN OTC DRUG LABEL
Date: 20200325

ACTIVE INGREDIENTS: ISOPROPYL ALCOHOL 0.7 mL/1 mL
INACTIVE INGREDIENTS: WATER; PROPYLENE GLYCOL; ALOE VERA LEAF; AMMONIUM ACRYLOYLDIMETHYLTAURATE

Hand Sanitizer Gel

DESCRIPTION

Hand Sanitizer Gel

Moisturizing with Aloe

Effective at eliminating more than 99.9% of many common harmful germs & bacteria in as little as 15 seconds.

Active ingredient

Isopropyl Alcohol 70% v/v

Purpose

Antimicrobial

Uses

Hand sanitizer to help reduce bacteria on the skin that could cause disease.

Recommended for repeated use.

Warnings

Flammable. Keep away from fire or flame.

For external use only

When using this product do not use in or near the eyes. In case of contact, rinse eyes thoroughly with water.

Stop use and ask a doctor if irritation or rash appears and lasts

Keep out of reach of children. If swallowed, get medical help or contact a Poison Control Center right away.

Directions

Place enough product in your palm to thoroughly cover your hands Rub hands together briskly until dry.

No rinsing required.

No towels needed .

Inactive ingredients

Water (Aqua), Aloe Vera, Propylene Glycol, Carboxethyl Acrylate Crosspolymer

Other information

Do not store above 110°F (43°C) May discolor certain fabrics or surfaces

Manufactured By: AgroChem, Inc 26 Freedom Way Saratoga Springs, NY 12866